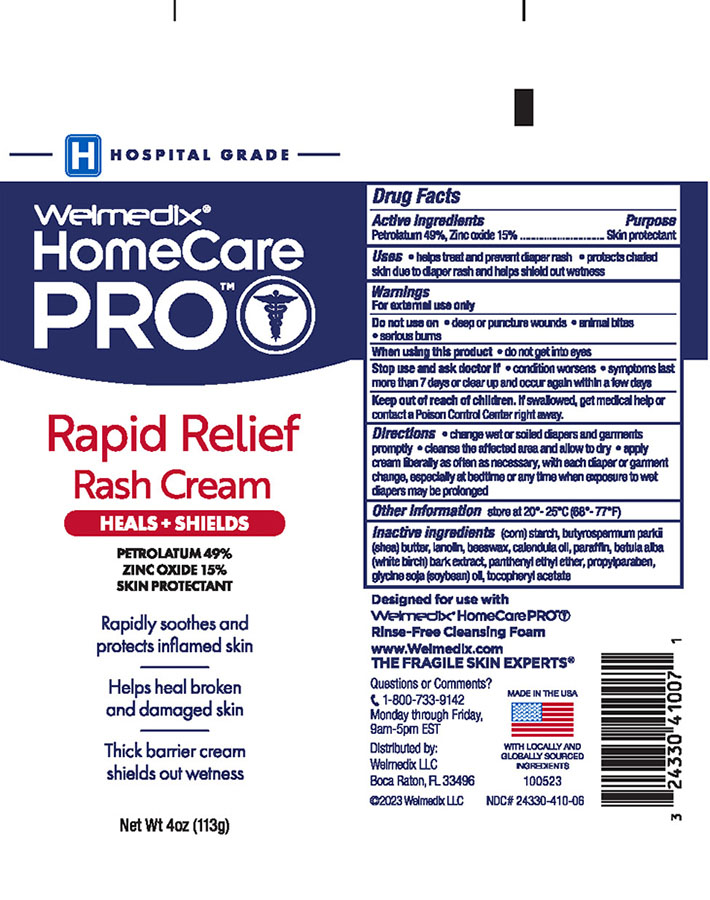 DRUG LABEL: Welmedix HomeCare PRO Extra Strength Rapid Rash Relief
NDC: 24330-410 | Form: CREAM
Manufacturer: Welmedix LLC
Category: otc | Type: HUMAN OTC DRUG LABEL
Date: 20231205

ACTIVE INGREDIENTS: PETROLATUM 49 g/100 g; ZINC OXIDE 15 g/100 g
INACTIVE INGREDIENTS: APIS CERANA WORKER SECRETION; BETULA PUBESCENS BARK; SHEA BUTTER; CALENDULA OFFICINALIS FLOWER; STARCH, CORN; SOY STEROL; LANOLIN; PANTHENYL ETHYL ETHER; PARAFFIN; PROPYLPARABEN; .ALPHA.-TOCOPHEROL ACETATE

Welmedix® HomeCare PRO Extra Strength Rapid Rash Relief Cream

Active ingredients

Petrolatum 49%
Zinc Oxide 15%

Purpose

Skin Protectant

Uses

- Protects against minor skin irritation due to diaper rash and helps seal out wetness
- Helps treat and prevent diaper rash

Warnings

For external use only

Stop use and ask doctor if

- condition worsens
- symptoms last more than 7 days or clear up and occur again within a few days

Keep out of reach of children.

If swallowed, get medical help or contact a Poison Control Center right away.

Directions:

• Change wet and soiled diapers, garments and linens promptly • Cleanse the affected area and allow to dry • Apply cream liberally, as often as necessary, with each diaper, garment or linen change, especially at bedtime or any time when exposure to wet or soiled diapers, garments, linens, feces or urine may be prolonged

Other Information:

Store at 20-25° C (68-77° F)

Inactive ingredients

(corn) starch, butyrospermum parkii (shea) butter, lanolin, beeswax, calendula oil, paraffin, betula alba (white birch) bark extract, panthenyl ethyl ether, propylparaben, glycine soja (soybean) oil, tocopheryl acetate

Principal Display Panel Tube

HEALS +
SHIELDS

Hospital
Grade

Welmedix®HomeCare
PRO

RAPID RELIEF
RASH CREAM

PETROLATUM 49%
ZINC OXIDE 15%

Immediately soothes
inflamed skin

Helps heal broken
and damaged skin

Thick barrier cream
seals out wetness

Net Wt 4 oz (113g)